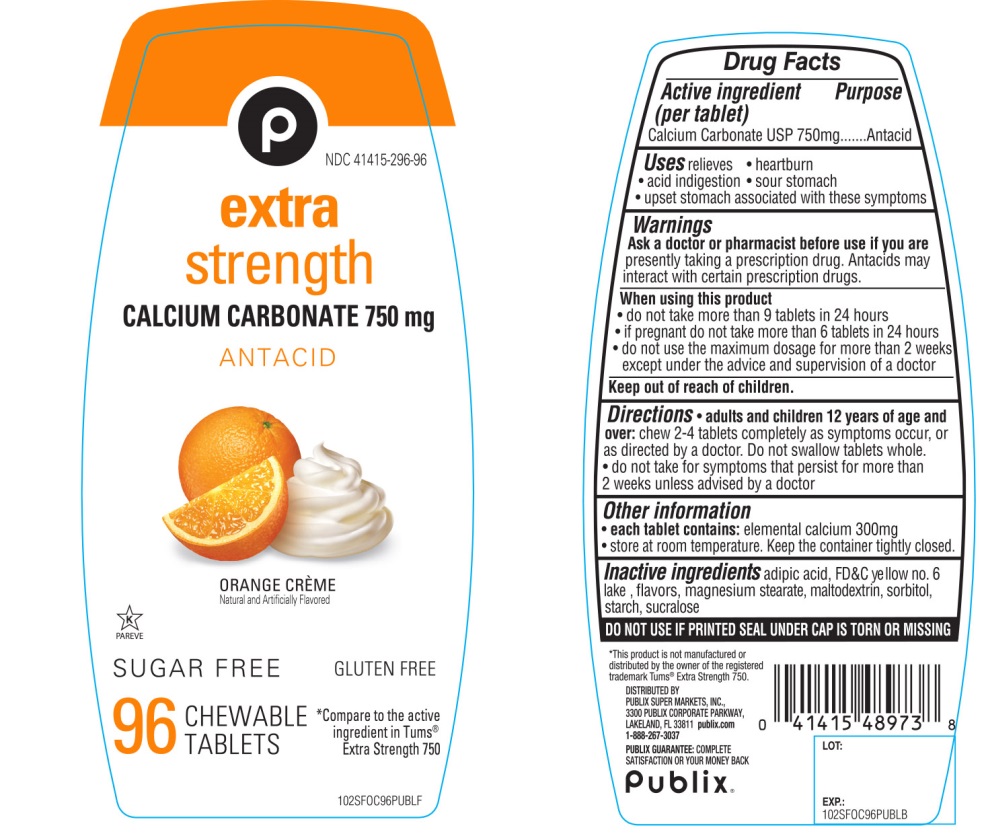 DRUG LABEL: Extra Strength Sugar Free

NDC: 41415-296 | Form: TABLET, CHEWABLE
Manufacturer: PUBLIX SUPER MARKETS, INC
Category: otc | Type: HUMAN OTC DRUG LABEL
Date: 20251028

ACTIVE INGREDIENTS: CALCIUM CARBONATE 750 mg/1 1
INACTIVE INGREDIENTS: ADIPIC ACID; FD&C YELLOW NO. 6; MAGNESIUM STEARATE; MALTODEXTRIN; SORBITOL; STARCH, CORN; SUCRALOSE

Extra Strength SUGAR FREE Antacid Tablets Calcium Carbonate 750 mg

Active ingredient (per tablet)

Calcium Carbonate USP 750 mg

Purpose

Antacid

Uses

relieves

- heartburn
- acid indigestion
- sour stomach
- upset stomach associated with these symptoms

Warnings

Ask a doctor or pharmacist before use if you arepresently taking a prescription drug. Antacids may interact with certain prescription drugs.

When using this product

- do not take more than 9 tablets in 24 hours
- If pregnant do not take more than 6 tablets in 24 hours
- do not use the maximum dosage for more than 2 weeks except under the advice and supervision of a doctor

Directions

- adults and children 12 years of age and over:chew 2-4 tablets as symptoms occur ,or as directed by a doctor. Do not swallow tablets whole.
- do not take for symptoms that persist for more than 2 weeks unless advised by a doctor

Other Information

- each tablet contains: elemental calcium 300 mg
- Store at room temperature. Keep the container tightly closed

Inactive ingredients

adipic acid, FD&C Yellow No. 6 Lake, flavors, magnesium stearate, maltodextrin, sorbitol, starch, sucralose,.

Questions or comments?

1-888-267-3037

SAFETY SEALED: DO NOT USE IF PRINTED SEAL UNDER CAP IS TORN OR MISSING

Package/Label Principal Display Panel

NDC 41415-296-96

*Compare to the active ingredient* Tums® Extra Strength 750

SUGAR FREE

Extra strength

CALCIUM CARBONATE 750 mg

ANTACID

ORANGE CRÈME

Naturally and Artificially Flavored

GLUTEN FREE

96 CHEWABLE TABLETS

K PARVE

DISTRIBUTED BY:

PUBLIX SUPER MARKETS, INC

3300 PUBLIX CORPORATE PARKWAY

LAKELAND, FL 33811 publix.com

1-888-267-3037

PUBLIX GUARANTEE: COMPLETE SATISFACTION OR YOUR MONEY BACK.

*This product is not manufactured or distributed by GlaxoSmithKline LLC, owner of the registered trademark, TUMS®Extra Strength.